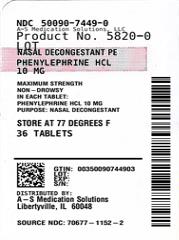 DRUG LABEL: NASAL DECONGESTANT PE
NDC: 50090-7449 | Form: TABLET, FILM COATED
Manufacturer: A-S Medication Solutions
Category: otc | Type: HUMAN OTC DRUG LABEL
Date: 20241113

ACTIVE INGREDIENTS: PHENYLEPHRINE HYDROCHLORIDE 10 mg/1 1
INACTIVE INGREDIENTS: CROSCARMELLOSE SODIUM; DEXTROSE MONOHYDRATE; CALCIUM PHOSPHATE, DIBASIC, DIHYDRATE; CURRY RED; LECITHIN, SOYBEAN; MAGNESIUM STEARATE; MALTODEXTRIN; CELLULOSE, MICROCRYSTALLINE; SILICA; CELLULOSE GUM; TRISODIUM CITRATE DIHYDRATE; CI 77891

NASAL DECONGESTANT PE

Active ingredient (in each tablet)

Phenylephrine HCl 10 mg

Purpose

Nasal decongestant

Uses

- temporarily relieves nasal congestion due to the common cold, hay fever or other upper respiratory allergies
- temporarily relieves sinus congestion and pressure

Warnings

Do not use

if you are now taking a prescription monoamine oxidase inhibitor (MAOI) (certain drugs for depression, psychiatric or emotional conditions, or Parkinson’s disease), or for 2 weeks after stopping the MAOI drug. If you do not know if your prescription drug contains an MAOI, ask a doctor or pharmacist before taking this product.

Ask a doctor before use if you have

- heart disease
- diabetes
- thyroid disease
- high blood pressure
- difficulty in urination due to enlargement of the prostate gland

When using this product

do not exceed recommended dosage.

Stop use and ask a doctor if

- nervousness, dizziness, or sleeplessness occur
- symptoms do not improve within 7 days or occur with fever

If pregnant or breast-feeding,

ask a health professional before use.

Keep out of reach of children.

In case of overdose, get medical help or contact a Poison Control Center right away.

Directions

- adults and children 12 years and over: take 1 tablet every 4 hours. Do not take more than 6 tablets in 24 hours.
- children under 12 years: ask a doctor

Other information

- TAMPER EVIDENT: DO NOT USE IF OUTER PACKAGE IS OPENED OR BLISTER IS TORN OR BROKEN
- store at 25°C (77°F); excursions permitted between 15°-30°C (59°-86°F)
- see end flap for expiration date and lot number

Inactive ingredients

croscarmellose sodium, dextrose monohydrate, dibasic calcium phosphate dihydrate, FD&C red #40, lecithin, magnesium stearate, maltodextrin, microcrystalline cellulose, silicon dioxide, sodium carboxymethylcellulose, sodium citrate dihydrate, titanium dioxide

Questions or comments?

Call 833-358-6431
Monday to Friday 9:00am to 7:00pm EST

HOW SUPPLIED

Product: 50090-7449

NDC: 50090-7449-0 18 TABLET, FILM COATED in a BLISTER PACK / 2 in a CARTON